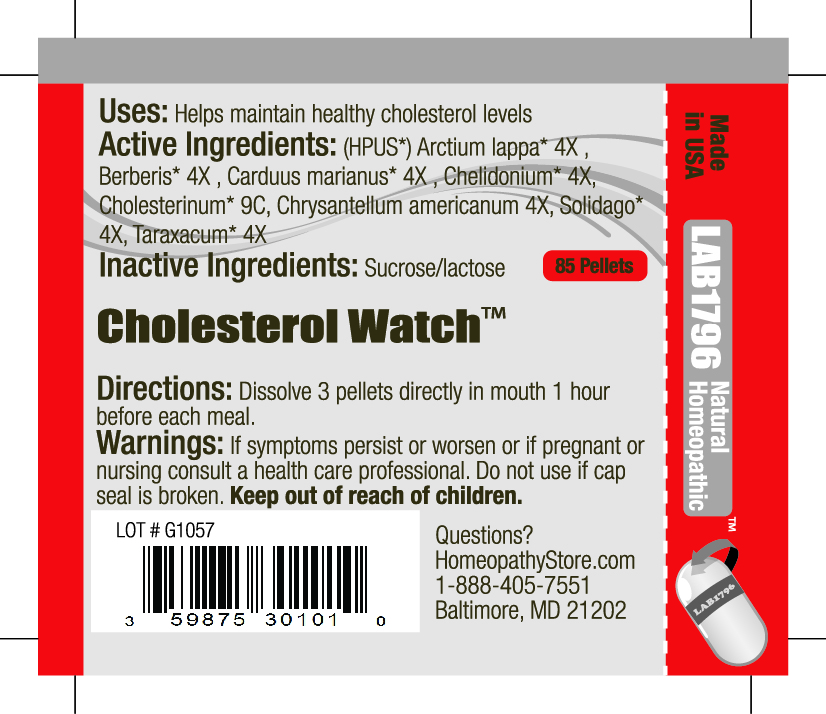 DRUG LABEL: Lab1796 Cholsterol Watch
NDC: 59875-3010 | Form: PELLET
Manufacturer: HomeopathyStore.com
Category: homeopathic | Type: HUMAN OTC DRUG LABEL
Date: 20101230

ACTIVE INGREDIENTS: ARCTIUM LAPPA ROOT 4 [hp_X]/1 1; BERBERIS VULGARIS ROOT BARK 4 [hp_X]/1 1; SILYBUM MARIANUM SEED 4 [hp_X]/1 1; CHELIDONIUM MAJUS 4 [hp_X]/1 1; CHOLESTEROL 9 [hp_C]/1 1; CHRYSANTHELLUM INDICUM SUBSP. AFROAMERICANUM 4 [hp_X]/1 1; SOLIDAGO VIRGAUREA FLOWERING TOP 4 [hp_X]/1 1; TARAXACUM OFFICINALE 4 [hp_X]/1 1
INACTIVE INGREDIENTS: SUCROSE; LACTOSE

Cholesterol Watch

Uses:

Helps maintain healthy cholesterol levels

Active Ingredients:

(HPUS*) Arctium lappa* 4X , Berberis* 4X , Carduus marianus* 4X, Chelidonium* 4X, Cholesterinum* 9C, Chrysantellum americanum 4X, Solidago* 4X, Taraxacum* 4X

Inactive Ingredients:

Sucrose/lactose

Directions:

DOSAGE AND ADMINISTRATION

Dissolve 3 pellets directly in mouth 1 hour before each meal.

Warnings:

If symptoms persist or worsen or if pregnant or nursing consult a health care professional. Do not use if cap seal is broken.

Keep out of reach of children.